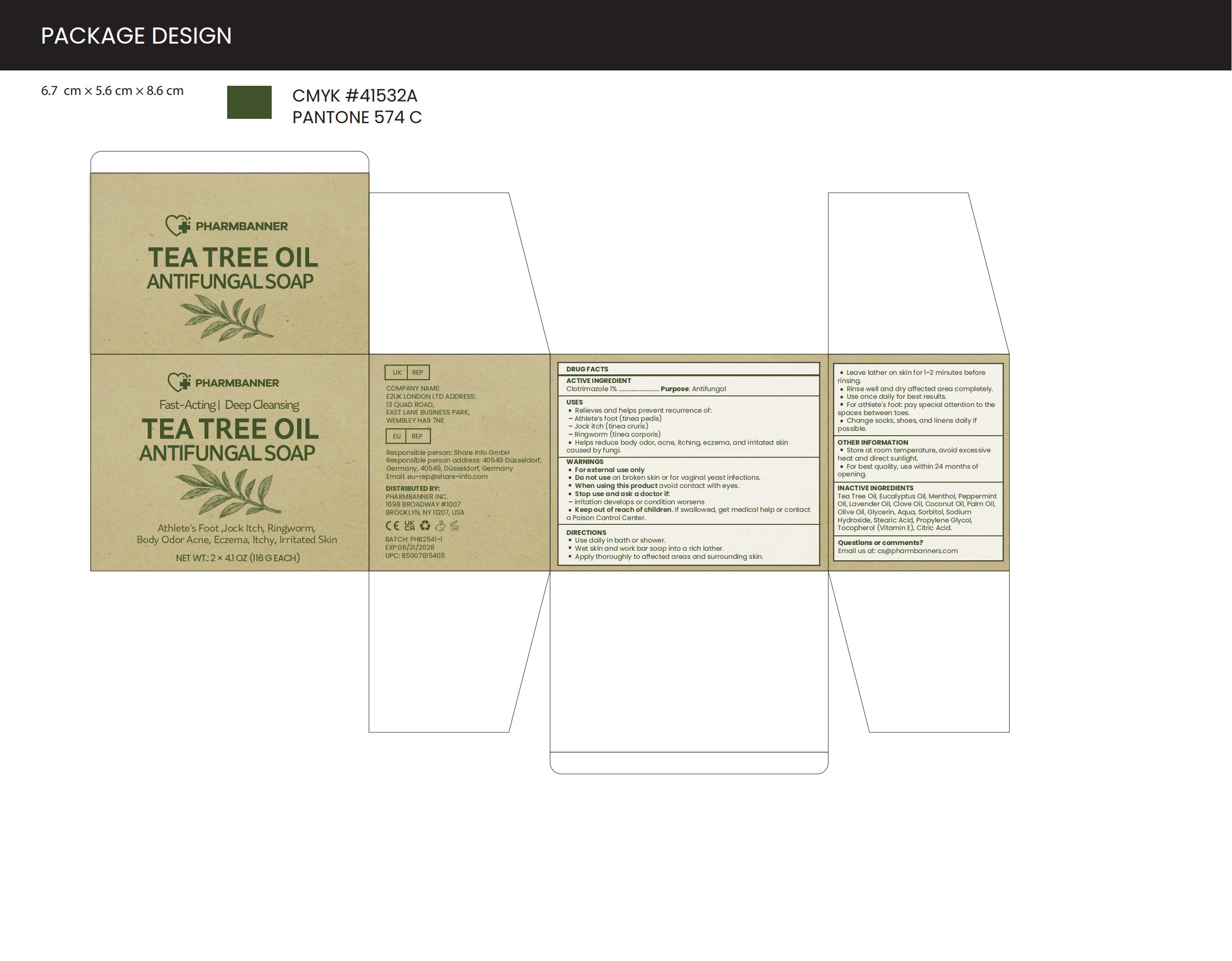 DRUG LABEL: PHARMBANNER Tea Tree Oil Antifungal Soap.
NDC: 83818-018 | Form: SOAP
Manufacturer: Shenzhen Xinxin Yunhai Technology Co., Ltd.
Category: otc | Type: HUMAN OTC DRUG LABEL
Date: 20250716

ACTIVE INGREDIENTS: CLOTRIMAZOLE 1 g/100 g
INACTIVE INGREDIENTS: AQUA; LAVENDER OIL; GLYCERIN; MENTHOL; STEARIC ACID; OLIVE OIL; PROPYLENE GLYCOL; EUCALYPTUS OIL; CITRIC ACID; SORBITOL; ALPHA-TOCOPHEROL; COCONUT OIL; TEA TREE OIL; PEPPERMINT OIL; CLOVE OIL; PALM OIL; SODIUM HYDROXIDE

83818-018

Active Ingredient

Clotrimazole 1%

Purpose

Antifungal

Use

■ Relieves and helps prevent recurrence of:
- Athlete's foot (tinea pedis)
- Jock itch (tinea cruris)
- Ringworm (tinea corporis)
■ Helps reduce body odor, acne, itching, eczema, and irritated skin caused by fungi.

Warnings

For external use only

Do not use

on broken skin or for vaginal yeast infections.

When Using

avoid contact with eyes

Stop Use

if irritation develops or condition worsens

Ask Doctor

if irritation develops or condition worsens

Keep Out Of Reach Of Children

If swallowed, get medical help or contact a Poison Control Center.

Directions

■ Use daily in bath or shower.
■ Wet skin and work bar soap into a rich lather.
■ Apply thoroughly to affected areas and surrounding skin.
■ Leave lather on skin for 1-2 minutes before rinsing.
■ Rinse well and dry affected area completely.
■ Use once daily for best results.
■ For athlete's foot: pay special attention to the spaces between toes.
■ Change socks, shoes, and linens daily if possible.

Other information

■ Store at room temperature, avoid excessive heat and direct sunlight.
■ For best quality, use within 24 months of opening.

Inactive ingredients

Tea Tree Oil, Eucalyptus Oil, Menthol, Peppermint Oil, Lavender Oil, Clove Oil, Coconut Oil, Palm Oil, Olive Oil, Glycerin, Aqua, Sorbitol, Sodium Hydroxide, Stearic Acid, Propylene Glycol, Tocopherol (Vitamin E), Citric Acid.

Questions

Email us: cs@pharmbanners.com